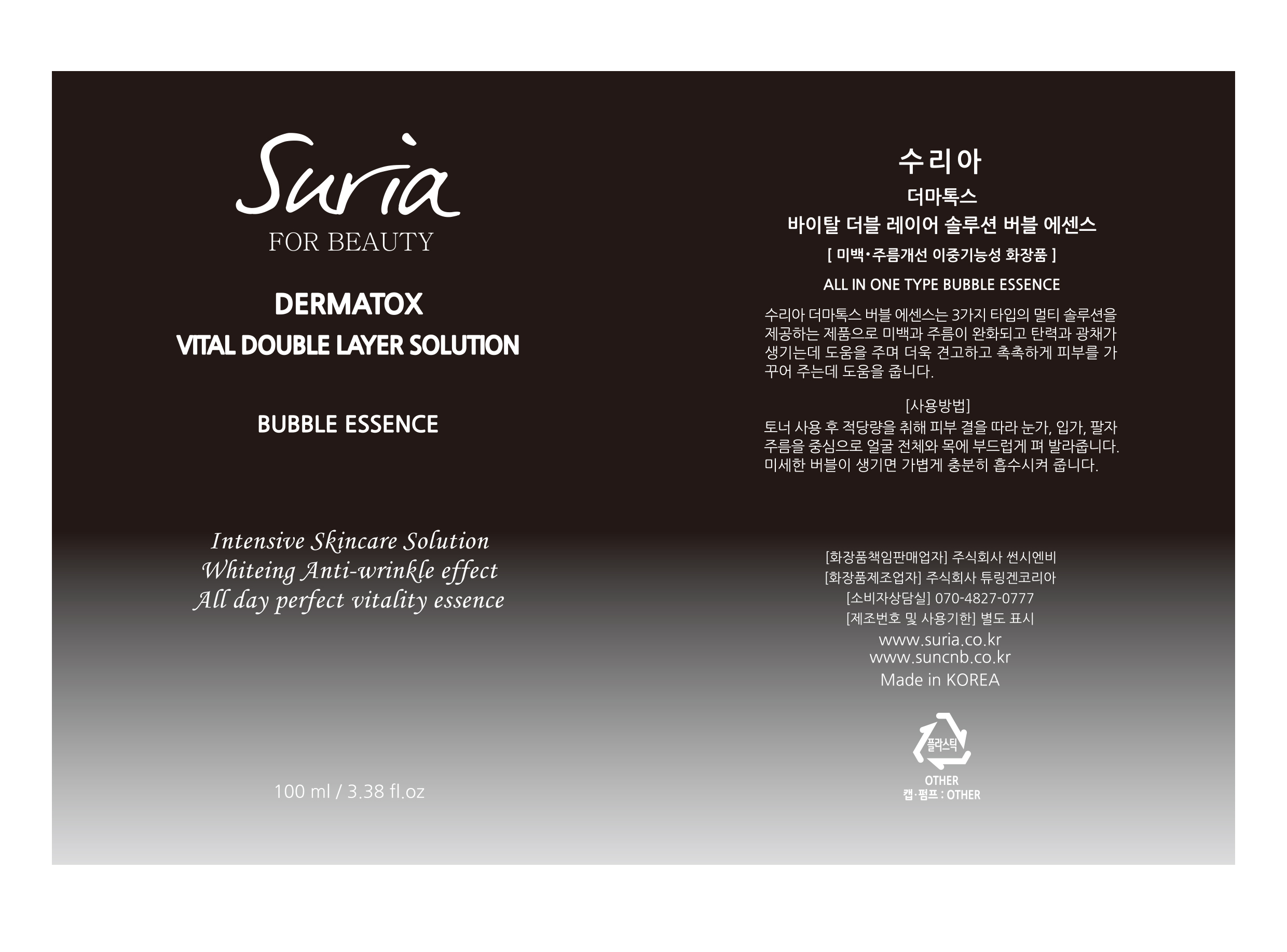 DRUG LABEL: SURIA BUBBLE ESSENCE
NDC: 81479-001 | Form: LIQUID
Manufacturer: SUN C&B
Category: otc | Type: HUMAN OTC DRUG LABEL
Date: 20210101

ACTIVE INGREDIENTS: METHYL PERFLUOROISOBUTYL ETHER 2 g/100 mL; GLYCERIN 2 g/100 mL
INACTIVE INGREDIENTS: WATER 96 g/100 mL

ACTIVE INGREDIENT

METHYL PERFLUOROISOBUTYL ETHER, GLYCERIN, WATER

INACTIVE INGREDIENT

Water,Etc

PURPOSE

Skin Protectant - Anti-Wrinkle, Whitening

Keep out of reach of the children

WARNINGS

1. If any of the following Symptoms occur, Cease use immediately. Continued usage would exacerbate the
symptoms. If symptoms persist, consult a doctor.
1) During of after usage, if red spots appear or you suffer from welling or itching or any other abnormal
symptoms after direct exposure to sunlight, consult a doctor immediately.
2)Avoid usage on cuts and wounds.
3) Storage and usage precautions.
A) Keep it out of reach of children.
B) Avoid exposure to direct sunlight during storage.

DOSAGE AND ADMINISTRATION

For external use only

INDICATIONS AND USAGE

Use a spatula to apply a proper amount to the face and pat the skin gently melting it by skin heat.